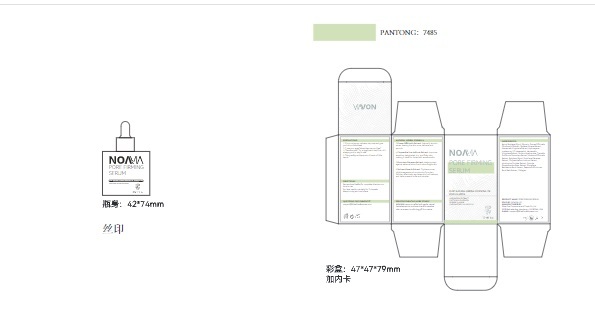 DRUG LABEL: NOAVIA Retinol Moisturizer
NDC: 85212-0011 | Form: CREAM
Manufacturer: Beijing JUNGE Technology Co., Ltd.
Category: otc | Type: HUMAN OTC DRUG LABEL
Date: 20250220

ACTIVE INGREDIENTS: TOCOPHEROL 1 g/100 mL; COLLAGENASE CLOSTRIDIUM HISTOLYTICUM 0.5 g/100 mL; CAFFEINE 5 g/100 mL; ASCORBIC ACID 1 g/100 mL; VITAMIN A 0.4 g/100 mL; RETINOL 1 g/100 mL
INACTIVE INGREDIENTS: ETHYLHEXYLGLYCERIN 0.1 mL/100 mL; MAGNOLIA OBOVATA BARK 0.1 mL/100 mL; MAGNOLIA BIONDII FLOWER 0.1 mL/100 mL; CAPRYLIC/CAPRIC TRIGLYCERIDE 2 mL/100 mL; DIMETHICONE 2 mL/100 mL; SODIUM HYALURONATE 0.1 mL/100 mL; PROPYLENE GLYCOL 3 mL/100 mL; NIACINAMIDE 3 mL/100 mL; HESPERIDIN 1 mL/100 mL; SQUALANE 3 mL/100 mL; CYCLOPENTASILOXANE 2 mL/100 mL; EDTA 0.2 mL/100 mL; HIBISCUS ESCULENTUS SEED EXTRACT 0.2 mL/100 mL; HYDROXYACETOPHENONE 0.1 mL/100 mL; ACETYL HEXAPEPTIDE-8 1 mL/100 mL; GLYCERIN 5 mL/100 mL; DIPEPTIDE DIAMINOBUTYROYL BENZYLAMIDE DIACETATE 1 mL/100 mL; ARGININE 1 mL/100 mL; FUCUS VESICULOSUS 1 mL/100 mL; EPIGALLOCATECHIN GALLATE 0.5 mL/100 mL; CARBOMER 1 mL/100 mL; 1,2-HEXANEDIOL 0.1 mL/100 mL; CENTELLA ASIATICA 0.5 mL/100 mL; BUTYLENE GLYCOL 0.5 mL/100 mL; AMMONIUM ACRYLOYLDIMETHYLTAURATE/VP COPOLYMER 1 mL/100 mL; CYCLOHEXASILOXANE 1 mL/100 mL; PERILLA OCYMOIDES SEED OIL 1 mL/100 mL; SCLEROTIUM GUM 0.2 mL/100 mL; FULLERENES 0.1 mL/100 mL; AQUA 57.3 mL/100 mL; BUTYROSPERMUM PARKII (SHEA) BUTTER 2 mL/100 mL

PURPOSE

Skin Protectant

INSTRUCTIONS FOR USE

Temporarily protects and helps relieve dry or cracked skin
Beneficlal for face, hands, body, and legs

WARNINGS

For external use only. Do not useon damaged or broken skin. Do not use on individuals aged 12 and under. When using this productavoid contact with eyes.

KEEP OUT OF REACH OF CHILDREN

In case of accidental ingestion, seek medical advice immediately orcontact a Poison Control Center right away.

REMS MEDICATION GUIDE

After cleansing, gently massage a pea-sized amount of cream onto the skin. Use twice a day, in the morning and evening.

OTHER SAFETY INFORMATION

store in a cool dry place, away from direct sunlight.

ACTIVE INGREDIENT

CAFFEINE,ASCORBIC ACID,TOCOPHEROL,RETINOL,HYDROLYZED COLLAGEN,Vitamin A

INACTIVE INGREDIENT

AQUA
GLYCERIN
PROPYLENE GLYCOL
NIACINAMIDE
SQUALANE
CYCLOPENTASILOXANE
CAPRYLIC/CAPRIC TRIGLYCERIDE
DIMETHICONE
BUTYROSPERMUM PARKII (SHEA BUTTER)
AMMONIUM ACRYLOYLDIMETHYLTAURATE/VP COPOLYMER
CYCLOHEXASILOXANE
HESPERIDIN
PERILLA OCYMOIDES LEAF EXTRACT
ACETYL HEXAPEPTIDE-8
DIPEPTIDE DIAMINOBUTYROYL BENZYLAMIDE DIACETATE
ARGININE/LYSINE POLYPEPTIDE
CARBOMER
FUCUS VESICULOSUS EXTRACT
BUTYLENE GLYCOL
EPIGALLOCATECHIN GALLATE
CENTELLA ASIATICA EXTRACT
HYDROLYZED SCLEROTIUM GUM
DISODIUM EDTA
HYDROLYZED HIBISCUS ESCULENTUS EXTRACT
1,2-HEXANEDIOL
HYDROXYACETOPHENONE
SODIUM HYALURONATE
FULLERENES
MAGNOLIA OBOVATA BARK EXTRACT
MAGNOLIA BIONDII FLOWER EXTRACT
ETHYLHEXYLGLYCERIN

DOSAGE AND ADMINISTRATION

50ml/1.76fl.oz

INDICATIONS AND USAGE

【Energized Skin with Enhanced Elasticity】:Caffeine stimulates mcirculation to firm and tighten the skin. By energizing the dermal layers, it supports collagen production, visibly lifting sagging areas and delivering a refreshed, sculpted appearance.
【Hydration Redefined for Lasting Glow】:Hyaluronic acid, known for its exceptional moisture-retention properties, replenishes hydration deep within the skin, plumping its surface for a smooth, dewy finish. Collagen reinforces the skin’s structural matrix, improving elasticity and helping retain hydration for a luminous, healthy glow.
【Naturally Powered, Transformative Results】:Infused with pure natural ingredients, NOAVIA’s anti-aging cream works at the cellular level to rejuvenate and repair. In just 4–8 weeks of consistent use, it reveals firmer, skin that reflects timeless elegance.